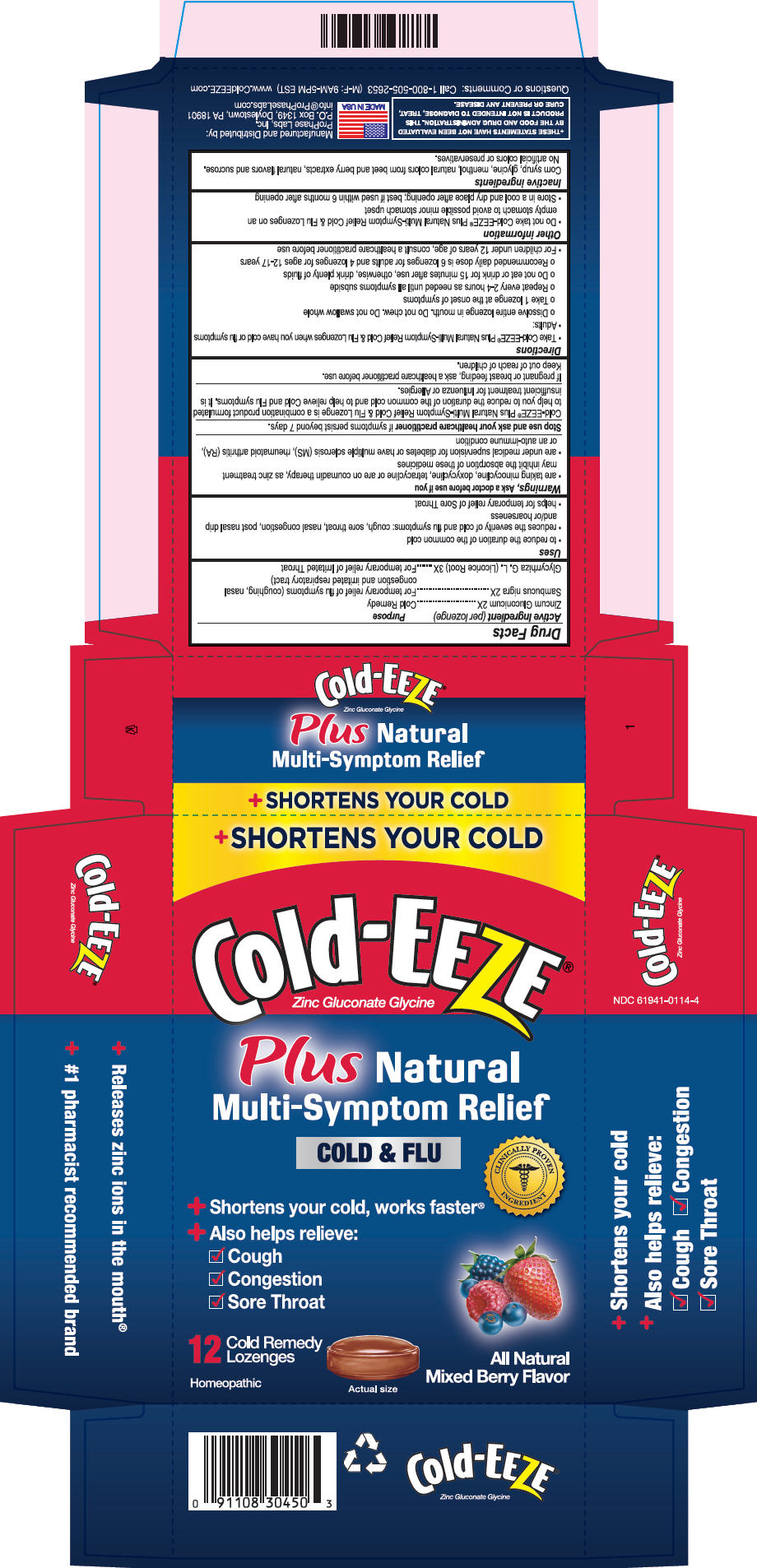 DRUG LABEL: Cold-EEZE 
NDC: 61941-0114 | Form: LOZENGE
Manufacturer: ProPhase Labs, Inc.
Category: homeopathic | Type: HUMAN OTC DRUG LABEL
Date: 20160127

ACTIVE INGREDIENTS: Zinc Gluconate 2 [hp_X]/1 1; Sambucus Nigra Flower 2 [hp_X]/1 1; Glycyrrhiza Glabra Leaf 3 [hp_X]/1 1
INACTIVE INGREDIENTS: Corn Syrup; Glycine; Menthol, Unspecified Form; Sucrose

Cold-EEZE®
Plus Natural Multi-Symptom Relief

Drug Facts

ACTIVE INGREDIENT

Active Ingredient (per lozenge) | Purpose
Zincum Gluconicum 2X | Cold Remedy
Sambucus nigra 2X | For temporary relief of flu symptoms (coughing, nasal congestion and irritated respiratory tract)
Glycyrrhiza G. L. (Licorice Root) 3X | For temporary relief of Irritated Throat

Uses

- to reduce the duration of the common cold
- reduces the severity of cold and flu symptoms: cough, sore throat, nasal congestion, post nasal drip and/or hoarseness
- helps for temporary relief of Sore Throat

Warnings

Ask a doctor before use if you

- are taking minocycline, doxycycline, tetracycline or are on coumadin therapy, as zinc treatment may inhibit the absorption of these medicines
- are under medical supervision for diabetes or have multiple sclerosis (MS), rheumatoid arthritis (RA), or an auto-immune condition

Stop use and ask your healthcare practitioner if symptoms persist beyond 7 days.

Cold-EEZE® Plus Natural Multi-Symptom Relief Cold & Flu Lozenge is a combination product formulated to help you to reduce the duration of the common cold and to help relieve Cold and Flu symptoms. It is insufficient treatment for Influenza or Allergies.

PREGNANCY OR BREAST FEEDING

If pregnant or breast feeding, ask a healthcare practitioner before use.

Keep out of reach of children.

Directions

- Take Cold-EEZE® Plus Natural Multi-Symptom Relief Cold & Flu Lozenges when you have cold or flu symptoms
- Adults:
  - Dissolve entire lozenge in mouth. Do not chew. Do not swallow whole
  - Take 1 lozenge at the onset of symptoms
  - Repeat every 2-4 hours as needed until all symptoms subside
  - Do not eat or drink for 15 minutes after use, otherwise, drink plenty of fluids
  - Recommended daily dose is 6 lozenges for adults and 4 lozenges for ages 12-17 years
- For children under 12 years of age, consult a healthcare practitioner before use

Other information

- Do not take Cold-EEZE® Plus Natural Multi-Symptom Relief Cold & Flu Lozenges on an empty stomach to avoid possible minor stomach upset
- Store in a cool and dry place after opening; best if used within 6 months after opening

Inactive ingredients

Corn syrup, glycine, menthol, natural colors from beet and berry extracts, natural flavors and sucrose. No artificial colors or preservatives.

Questions or Comments

Call 1-800-505-2653 (M-F: 9AM-5PM EST)

Manufactured and Distributed by:
ProPhase Labs, Inc.
P.O. Box 1349, Doylestown, PA 18901

PRINCIPAL DISPLAY PANEL - 12 Lozenge Package

+ SHORTENS YOUR COLD

Cold-EEZE®
Zinc Gluconate Glycine

Plus Natural
Multi-Symptom Relief

COLD & FLU

CLINICALLY PROVEN
INGREDIENT

+ Shortens your cold, works faster®
+ Also helps relieve:
  ✓ Cough
  ✓ Congestion
  ✓ Sore Throat

12
Cold Remedy
Lozenges

Homeopathic

Actual size

All Natural
Mixed Berry Flavor